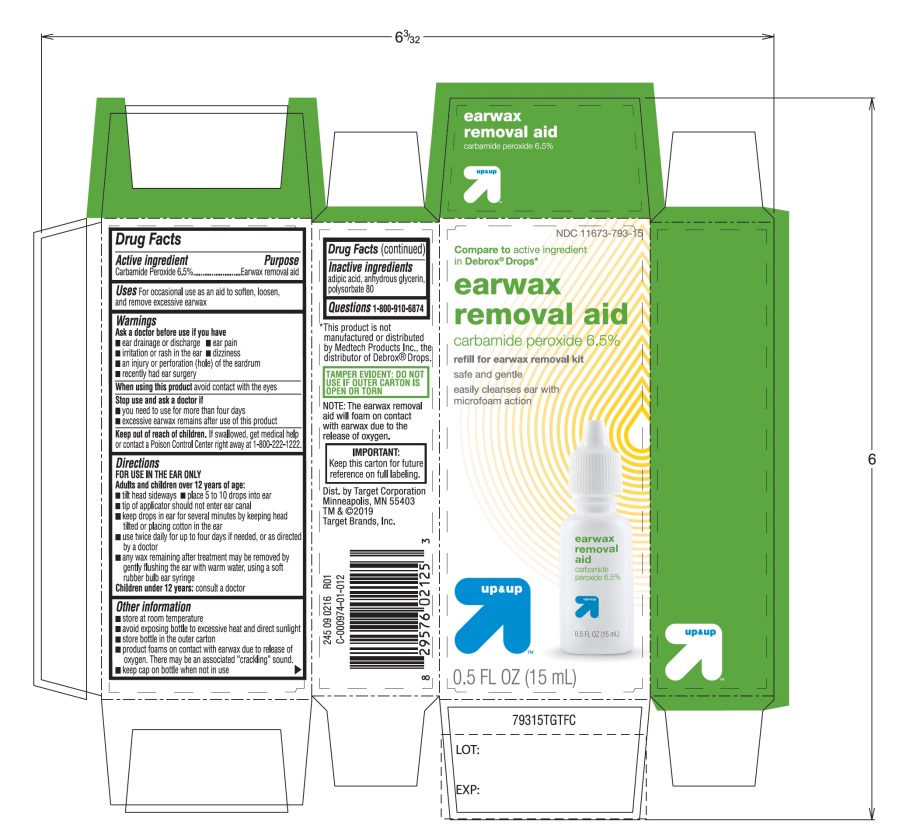 DRUG LABEL: Ear Wax Removal Aid Drops
NDC: 11673-793 | Form: LIQUID
Manufacturer: Target Corporation
Category: otc | Type: HUMAN OTC DRUG LABEL
Date: 20251105

ACTIVE INGREDIENTS: CARBAMIDE PEROXIDE 0.065 mg/1 mL
INACTIVE INGREDIENTS: ADIPIC ACID; GLYCERIN; POLYSORBATE 80

Target Ear Wax Removal Aid Drops

Drug Facts

Active ingredient

Carbamide peroxide 6.5%

Purpose

Earwax removal aid

Uses

For occasional use as an aid to soften, loosen and remove excessive ear wax

Warnings

Ask a doctor before use

- if you have ear drainage or discharge
- ear pain
- irritation or rash in the ear
- dizziness
- an injury or perforation (hole) of the eardrum
- recently had ear surgery

When using this product

avoid contact with the eyes

Stop use and ask a doctor if

- you need to use for more than four days
- excessive ear wax remains after use this product

Keep out of reach of children.

If swallowed, get medical help or contact a Poison Control Center (1-800-222-1222) right away.

Directions

FOR USE IN THE EAR ONLY.

- Adults and children over 12 years of age:
- tilt head sideways
- place 5 to 10 drops into ear canal.
- tip of applicator should not enter ear canal.
- keep drops in ear for several minutes by keeping head tilted or placing cotton in the ear.
- Use twice daily for up to 4 days if needed, or as directed by a doctor.
- Any wax remaining after treatment may be removed by gently flushing the ear with warm water, using a soft rubber bulb ear syringe.

Children under 12 years of age:consult a doctor.

Other information

- Store at room temperature
- Avoid exposing bottle to excessive heat and direct sunlight
- Store bottle in the outer carton
- Product foams on contact with earwax due to release of oxygen. There may be an associated “cracking” sound.
- Keep cap on bottle when not in use

Inactive ingredients

adipic acid, anhydrous glycerin, polysorbate 80.

PRINCIPAL DISPLAY PANEL

NDC 11673-793-15

*Compare to the active ingredient in Debrox®Drops

Ear Wax Removal kit
Carbamide Peroxide 6.5%

Ear Wax Removal Aid

Safe & Gentle

Microfoam Cleansing Action

Easy to use Instructions
NET WT 0.5 FL OZ (15 mL)

Kit includes soft rubber bulb ear syringe and drops

TAMPER EVIDENT: DO NOT USE IF OUTER CARTON IS OPEN OR TORN

The up & up earwax removal kit cleanses the ear with foaming action, providing a safe, non-irritating method of softening and removing earwax.

NOTE: The earwax removal drops will foam on contact with earwax due to the release of oxygen.

IMPORTANT: Keep the carton for future reference on full labeling.

100% satisfaction guaranteed or your money back.

Dist. By Target Corp.

Minneapolis, MN 55403

TM & ©2019 Target Brands, Inc.

*This product is not manufactured or distributed by Medtech Products Inc. the distributor of Debrox®Drops.